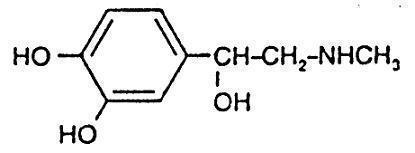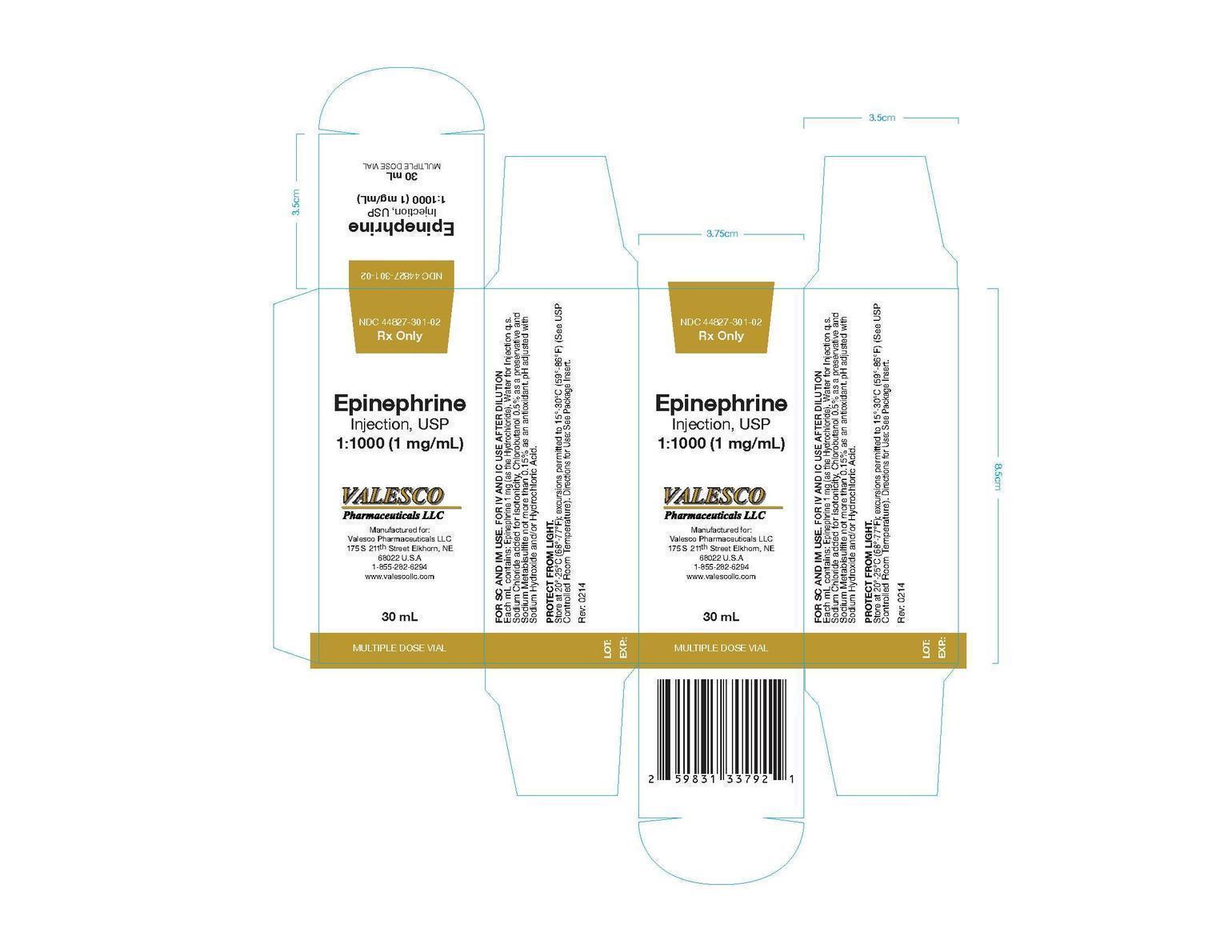 DRUG LABEL: Epinephrine
NDC: 44827-301 | Form: INJECTION, SOLUTION
Manufacturer: Valesco Pharmaceuticals LLC.
Category: prescription | Type: HUMAN PRESCRIPTION DRUG LABEL
Date: 20140224

ACTIVE INGREDIENTS: EPINEPHRINE HYDROCHLORIDE 1 mg/1 mL
INACTIVE INGREDIENTS: SODIUM CHLORIDE; CHLOROBUTANOL; SODIUM METABISULFITE; WATER

1:1000

Rx only

DESCRIPTION

Epinephrine Injection, USP is a sterile, nonpyrogenic solution intended for subcutaneous or intramuscular injection. When diluted, it may also be administered intracardially or intravenously. Each mL contains: Epinephrine 1 mg (as the Hydrochloride), Water for Injection q.s. Sodium Chloride added for isotonicity, Chlorobutanol 0.5% (a chloroform derivative) as a preservative and Sodium Metabisulfite not more than 0.15% as an antioxidant. Epinephrine is the active principle of the adrenal medulla, chemically described as (-)-3,4-Dihydroxy-α-[(methylamino)methyl)]benzyl alcohol, and has the following structural formula:

CLINICAL PHARMACOLOGY

Epinephrine is a sympathomimetic drug. It activates an adrenergic receptive mechanism on effector cells and imitates all actions of the sympathetic nervous system except those on the arteries of the face and sweat glands. Epinephrine acts on both alpha and beta receptors and is the most potent alpha receptor activator.

INDICATIONS AND USAGE

In general, the most common uses of epinephrine are to relieve respiratory distress due to bronchospasm, to provide rapid relief of hypersensitivity reactions to drugs and other allergens, and to prolong the action of infiltration anesthetics. Its cardiac effects may be of use in restoring cardiac rhythm in cardiac arrest due to various causes, but it is not used in cardiac failure or in hemorrhagic, traumatic, or cardiogenic shock.

Epinephrine is used as a hemostatic agent. It is also used in treating mucosal congestion of hay fever, rhinitis and acute sinusitis; to relieve bronchial asthmatic paroxysms; in syncope due to complete heart block or carotid sinus hypersensitivity; for symptomatic relief of serum sickness, urticaria, angioneurotic edema; for resuscitation in cardiac arrest following anesthetic accidents; in simple (open angle) glaucoma; for relaxation of uterine musculature and to inhibit uterine contractions. Epinephrine injection can be utilized to prolong the action of local anesthetics (see CONTRAINDICATIONS).

CONTRAINDICATIONS

Epinephrine is contraindicated in narrow angle (congestive) glaucoma, shock, during general anesthesia with halogenated hydrocarbons or cyclopropane and in individuals with organic brain damage. Epinephrine is also contraindicated with local anesthesia of certain areas, e.g., fingers, toes, because of the danger of vasoconstriction producing sloughing of tissue; in labor because it may delay the second stage; in cardiac dilatation and coronary insufficiency.

WARNINGS

Administer with caution to elderly people; to those with cardiovascular disease, hypertension, diabetes, or hyperthyroidism; in psychoneurotic individuals; and in pregnancy.

Patients with long-standing bronchial asthma and emphysema who have developed degenerative heart disease should be administered the drug with extreme caution.

Overdosage or inadvertent intravenous injection of epinephrine may cause cerebrovascular hemorrhage resulting from the sharp rise in blood pressure.

Fatalities may also result from pulmonary edema because of the peripheral constriction and cardiac stimulation produced. Rapidly acting vasodilators, such as nitrites, or alpha blocking agents may counteract the marked pressor effects of epinephrine.

Epinephrine is the preferred treatment of serious allergic or other emergency situations even though this product contains sodium metabisulfite, a sulfite that may in other products cause allergic-type reactions including anaphylactic symptoms or life-threatening or less severe asthmatic episodes in certain susceptible persons. The alternative to using epinephrine in a life-threatening situation may not be satisfactory. The presence of a sulfite in this product should not deter administration of the drug for treatment of serious allergic or other emergency situations.

PRECAUTIONS

General

Epinephrine injection should be protected from exposure to light. Do not remove vial from carton until ready to use. The solution should not be used if it is pinkish or darker than slightly yellow or if it contains a precipitate.

Epinephrine is readily destroyed by alkalies and oxidizing agents. In the latter category are oxygen, chlorine, bromine, iodine, permanganates, chromates, nitrites, and salts of easily reducible metals, especially iron.

Drug Interactions

Use of epinephrine with excessive doses of digitalis, mercurial diuretics, or other drugs that sensitize the heart to arrhythmias is not recommended. Anginal pain may be induced when coronary insufficiency is present.

The effects of epinephrine may be potentiated by tricyclic antidepressants; certain antihistamines, e.g., diphenhydramine, tripelennamine, d-chlorpheniramine, and sodium l-thyroxine.

Pregnancy

Teratogenic Effects

Pregnancy Category C. Epinephrine has been shown to be teratogenic in rats when given in doses about 25 times the human dose. There are no adequate and well-controlled studies in pregnant women. Epinephrine should be used during pregnancy only if the potential benefit justifies the potential risk to the fetus.

ADVERSE REACTIONS

Transient and minor side effects of anxiety, headache, fear, and palpitations often occur with therapeutic doses, especially in hyperthyroid individuals. Repeated local injections can result in necrosis at sites of injection from vascular constriction. “Epinephrine-fastness” can occur with prolonged use.

DOSAGE AND ADMINISTRATION

Subcutaneously or intramuscularly − 0.2 to 1 mL (mg). Start with a small dose and increase if required.

Note: The subcutaneous is the preferred route of administration. If given intramuscularly, injection into the buttocks should be avoided.

For bronchial asthma and certain allergic manifestations, e.g., angioedema, urticaria, serum sickness, anaphylactic shock, use epinephrine subcutaneously. For bronchial asthma in pediatric patients, administer 0.01 mg/kg or 0.3 mg/m2 to a maximum of 0.5 mg subcutaneously, repeated every four hours if required.

For cardiac resuscitation − A dose of 0.5 mL (0.5 mg) diluted to 10 mL with sodium chloride injection can be administered intravenously or intracardially to restore myocardial contractility. External cardiac massage should follow intracardial administration to permit the drug to enter coronary circulation. The drug should be used secondarily to unsuccessful attempts with physical or electromechanical methods.

Store at 20°-25°C (68°-77°F); excursions permitted to 15°-30°C (59°-86°F) (See USP Controlled Room Temperature).

Protect from light.

Parenteral drug products should be inspected visually for particulate matter and discoloration whenever solution and container permit.

HOW SUPPLIED

Epinephrine Injection, USP 1:1000 (1mg/mL)

NDC 44827-301-02 30 mL Multiple Dose Vial

Rev 02/14